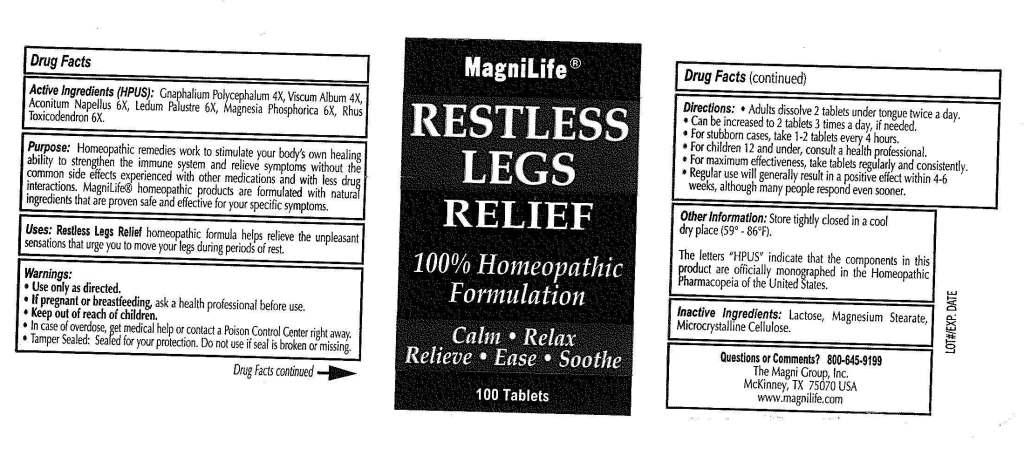 DRUG LABEL: Restless Legs Relief
NDC: 57520-0450 | Form: TABLET
Manufacturer: Apotheca Company
Category: homeopathic | Type: HUMAN OTC DRUG LABEL
Date: 20101111

ACTIVE INGREDIENTS: ACONITUM NAPELLUS 6 [hp_X]/1 1; PSEUDOGNAPHALIUM OBTUSIFOLIUM 4 [hp_X]/1 1; LEDUM PALUSTRE TWIG 6 [hp_X]/1 1; MAGNESIUM PHOSPHATE, DIBASIC TRIHYDRATE 6 [hp_X]/1 1; TOXICODENDRON PUBESCENS LEAF 6 [hp_X]/1 1; VISCUM ALBUM FRUITING TOP 4 [hp_X]/1 1
INACTIVE INGREDIENTS: LACTOSE; MAGNESIUM STEARATE; CELLULOSE, MICROCRYSTALLINE

Restless Legs Relief

ACTIVE INGREDIENT

ACTIVE INGREDIENTS: Aconitum napellus 6X, Gnaphalium polycephalum 4X, Ledum palustre 6X, Magnesia phosphorica 6X, Rhus toxicodendron 6X, Viscum album 4X.

PURPOSE

USES: Restless Legs Relief homeopathic formula helps relieve the unpleasant sensations that urge you to move your legs during periods of rest.

WARNINGS: Use only as directed.

If pregnant or breastfeeding, ask a health professional before use.

Keep out of reach of children.

In case of overdose, get medical help or contact a Poison Control Center right away.

Tamper sealed: Sealed for your protection. Do not use if seal is broken or missing.

Other Information: Store tightly closed in a cool dry place (59 to 86 F)

DOSAGE AND ADMINISTRATION

DIRECTIONS: Adults dissolve 2 tablets under tongue twice a day.

Can be increased to 2 tablets 3 times a day, if needed.

For stubborn cases, take 1-2 tablets every 4 hours.

For children 12 and under, consult a health professional.

For maximum effectiveness, take tablets regularly and consistently.

Regular use will generally result in a positive effect within 4-6 weeks, although many people respond even sooner.

INACTIVE INGREDIENT

INACTIVE INGREDIENTS: Lactose, Magnesium stearate, Mycrocrystalline cellulose.

KEEP OUT OF REACH OF CHILDREN. In case of overdose, get medical help or contact a Poison Control Center right away.

INDICATIONS AND USAGE

USES: Restless Legs Relief homeopathic formula helps relieve the unpleasant sensations that urge you to move your legs during periods of rest.

Questions or Comments? 800-645-9199

The Magni Group, Inc.

McKinney, TX 75070 USA

www.magnilife.com

PACKAGE LABEL

MagniLife

RESTLESS LEGS RELIEF

100% Homeopathic Formulation

Calm Relax Relieve Ease Soothe

100 Tablets